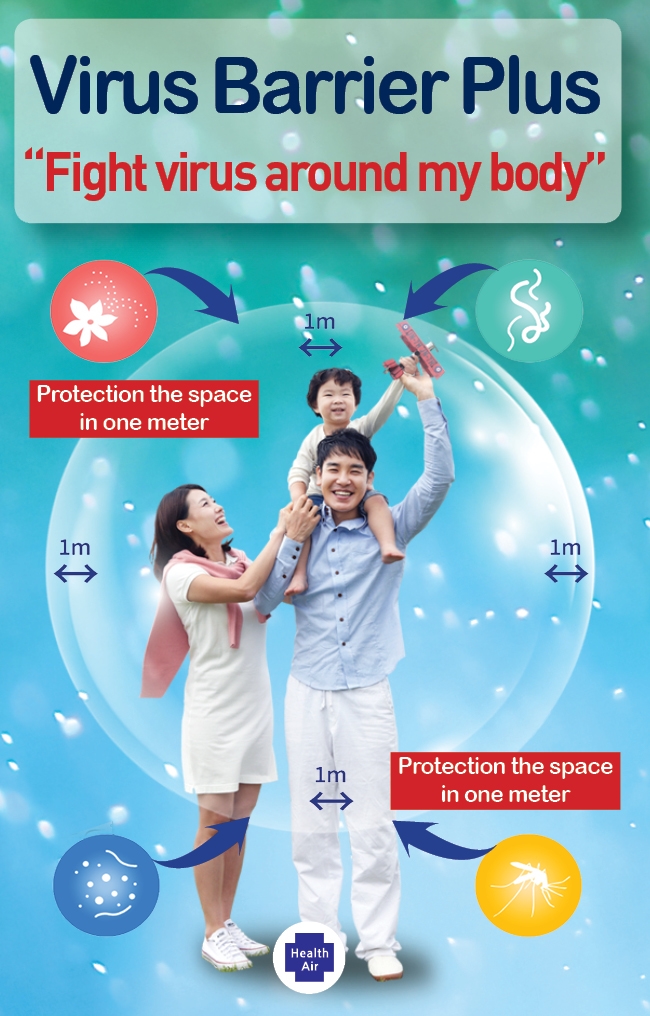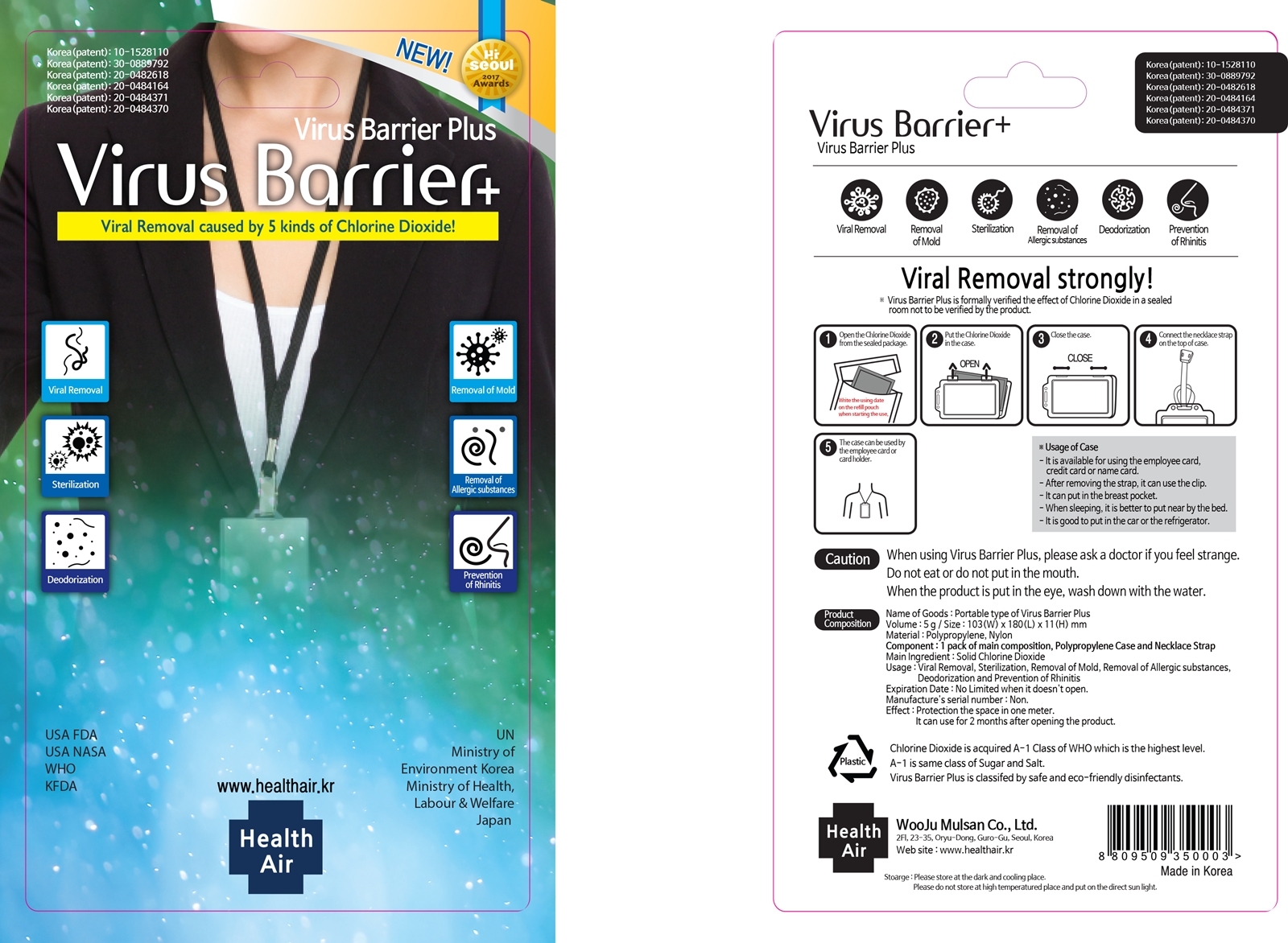 DRUG LABEL: VIRUS BARRIER PLUS
NDC: 79928-201 | Form: STICK
Manufacturer: Wooju Mulsan Co., Ltd
Category: otc | Type: HUMAN OTC DRUG LABEL
Date: 20200730

ACTIVE INGREDIENTS: SODIUM CHLORITE 20 g/100 g
INACTIVE INGREDIENTS: SODIUM HYDROXIDE; MAGNESIUM TRISILICATE

Active Ingredient

SODIUM CHLORITE 20%

Purpose

Viral Removal, Removal of Mold, Sterilization, Removal of Allergic substances, Deodorization, Prevention of Rhinitis

Usage of Case

- It is available for using the employee card, cerdit card or name card.

- After removing the strap, it can use the clip.

- It can put in the breast pocket.

- When sleeping, it is better to put near by the bed.

- It is good to put in the car or the refrigerator.

Caution

Do not eat or do not put in the mouth.

When the product is put in the eye, wash down with the water.

Caution

When using Virus Barrier Plus, please ask a doctor if you feel strange.

Caution

Keep out of reach of children.

Directions

1 Open the Chlorine Dioxide from the sealed package.

2 Put the Chlorine Dioxide in the case.

3 Close the case.

4 Connect the necklace strap on the top of case.

5 The case can be used by the employee card or card holder.

Inactive Ingredient

SEPIOLITE, SODIUM HYDROXIDE